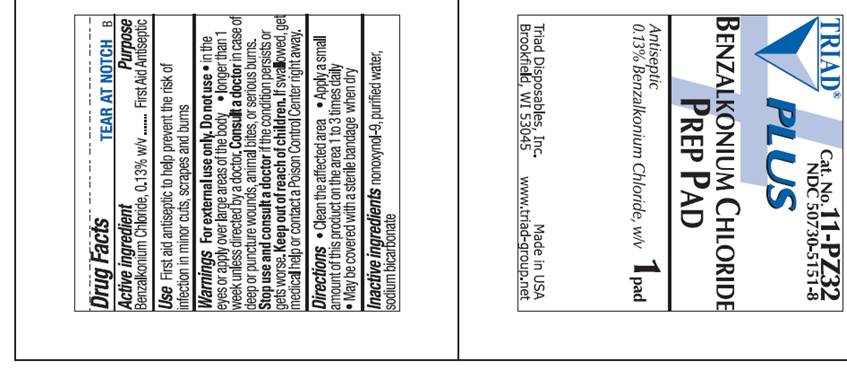 DRUG LABEL: BZK Plus Prep Pad
NDC: 50730-5151 | Form: SOLUTION
Manufacturer: H and P Industries, Inc. dba Triad Group
Category: otc | Type: HUMAN OTC DRUG LABEL
Date: 20091201

ACTIVE INGREDIENTS: benzalkonium chloride .0013 mL/1 1
INACTIVE INGREDIENTS: nonoxynol-9; sodium bicarbonate; water

DRUG FACTS

ACTIVE INGREDIENT

Benzalkonium chloride .13% w/v

PURPOSE

Antiseptic

USE

First Aid Antiseptic to help prevent the risk of infection in minor cuts, scrapes and burns

WARNINGS

For external use only.

Do not use

- in the eyes
- longer than 1 week unless directed by a doctor

Consult a doctor in case of

- deep or puncture wounds
- animal bites
- serious burns

Stop use and ask a doctor

if condition persists or gets worse

Keep out of reach of children

If swallowed, get medical help or contact a Poison Control Center right away.

DIRECTIONS

- clean the affected area
- apply a small amount of this product to the area 1-3 times daily
- may be covered with a sterile bandage when dry

INACTIVE INGREDIENTS

nonoxynol-9, purified water, sodium bicarbonate

POUCH INFORMATION

TRIAD PLUS
Cat. No. 11-PZ32
NDC 50730-5151-8
BENZALKONIUM CHLORIDE
PREP PAD
Antiseptic
0.13% Benzalkonium Chloride, w/v
1 Pad
Triad Disposables, Inc.
Brookfield, WI 53045
Made in USA
www.triad-group.net